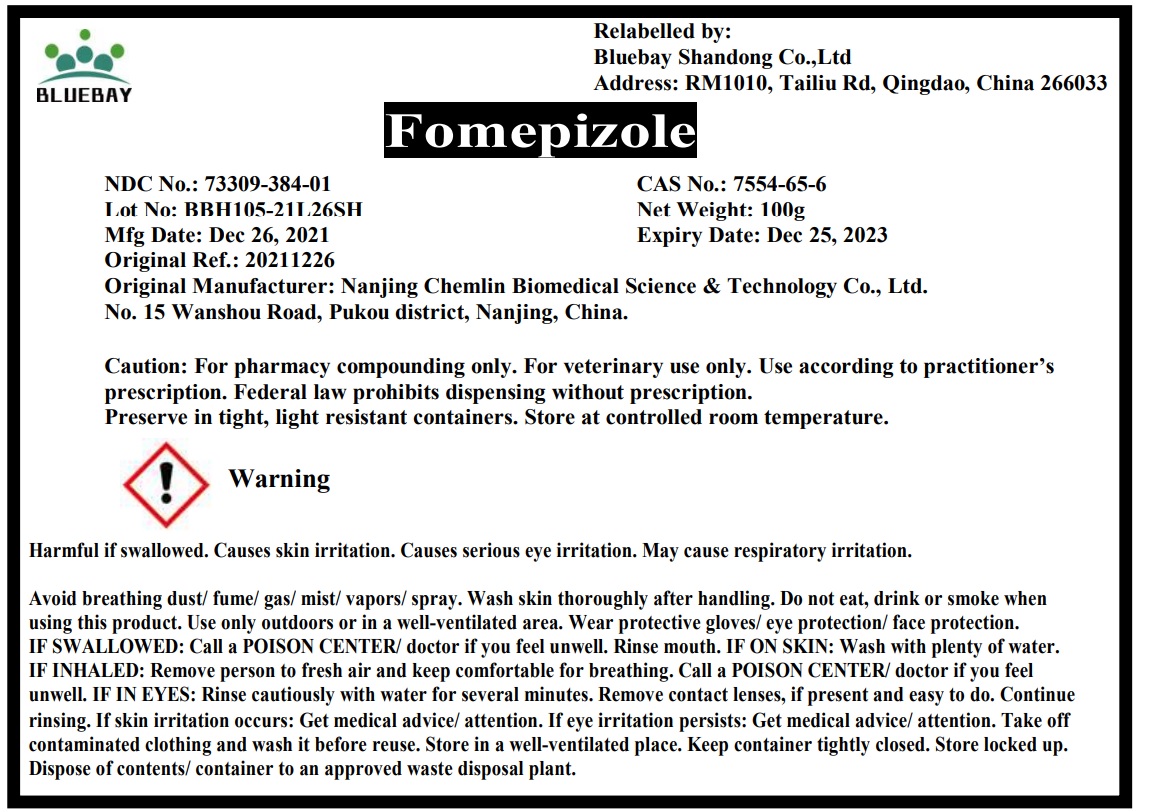 DRUG LABEL: Fomepizole
NDC: 73309-384 | Form: LIQUID
Manufacturer: BLUEBAY SHANDONG CO.,LTD
Category: other | Type: BULK INGREDIENT - ANIMAL DRUG
Date: 20220323

ACTIVE INGREDIENTS: Fomepizole 1 g/1 g

Fomepizole